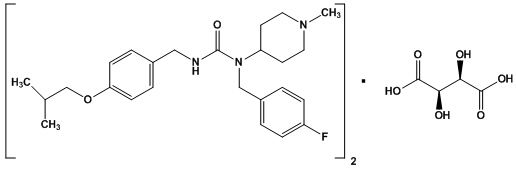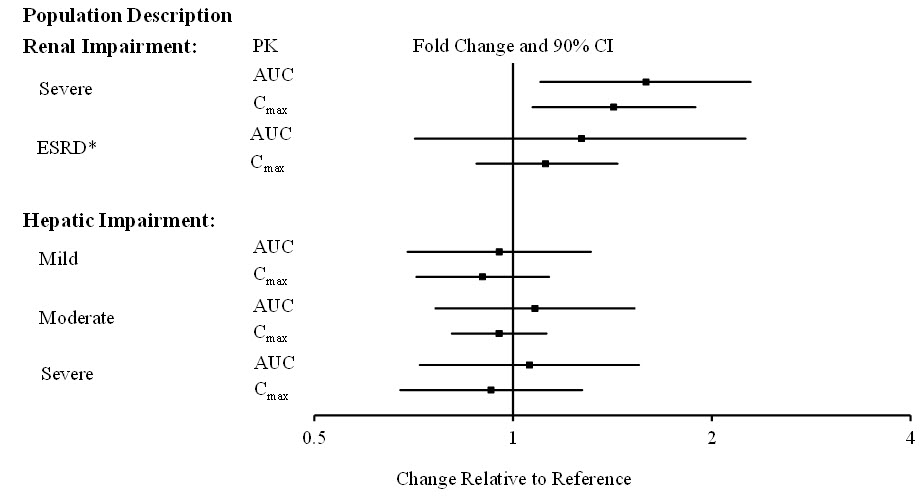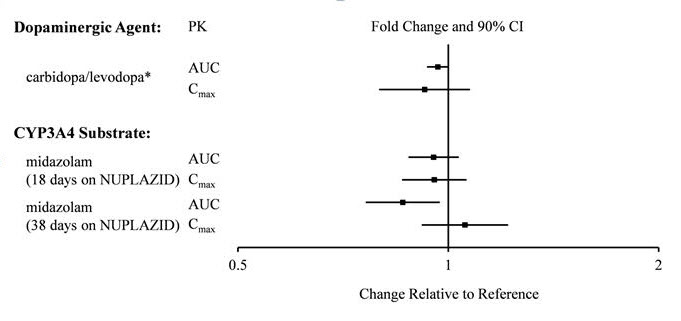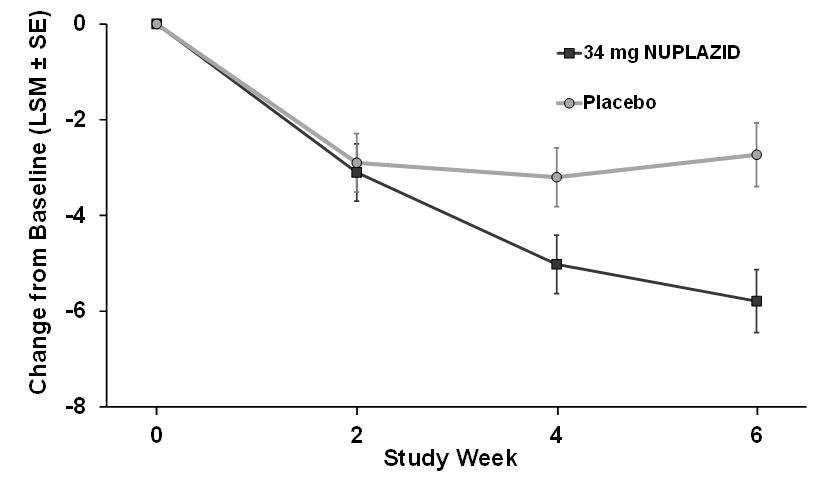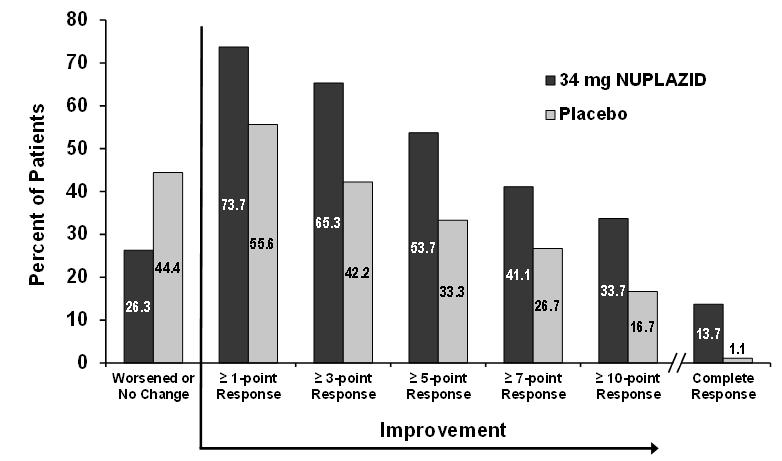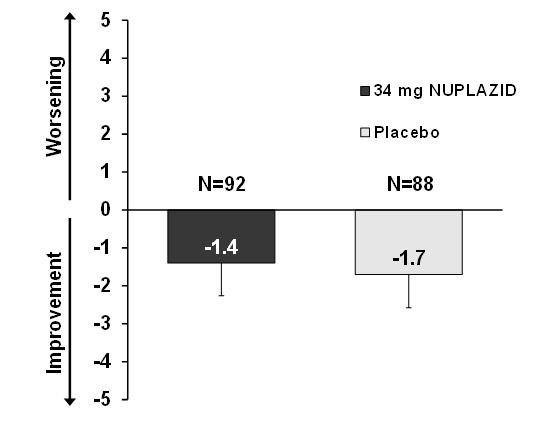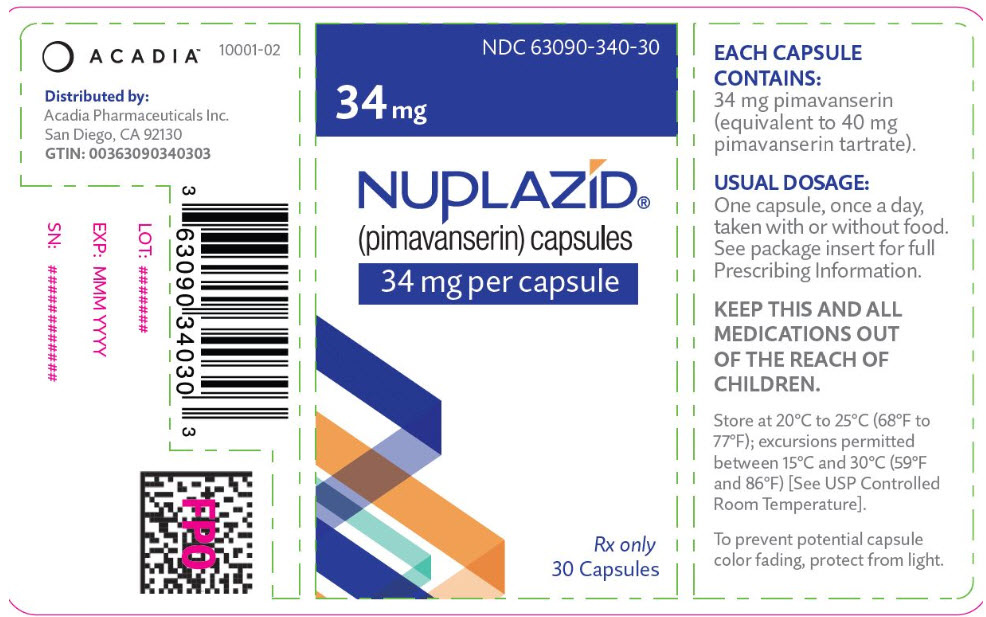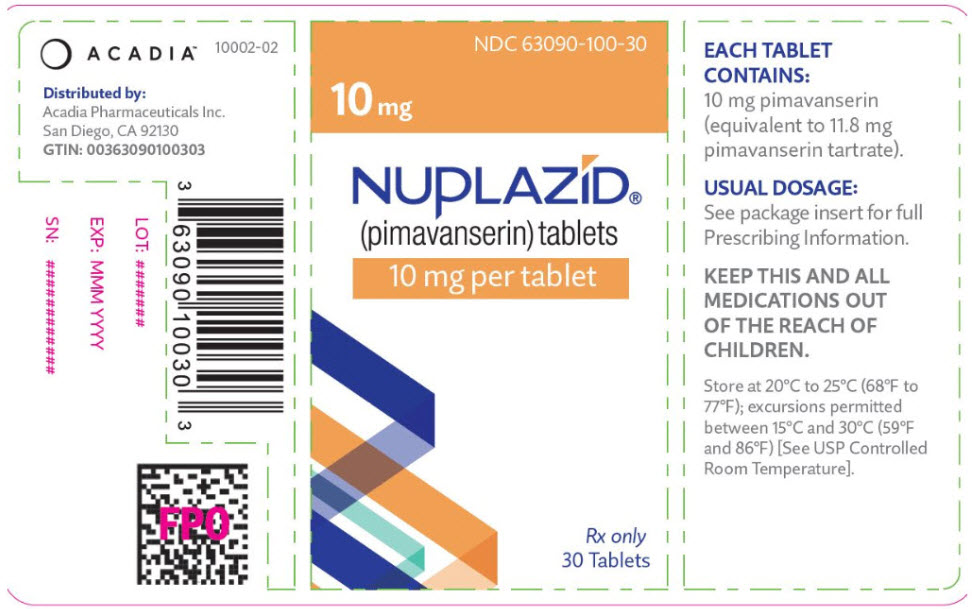 DRUG LABEL: NUPLAZID
NDC: 63090-340 | Form: CAPSULE
Manufacturer: Acadia Pharmaceuticals Inc.
Category: prescription | Type: HUMAN PRESCRIPTION DRUG LABEL
Date: 20250131

ACTIVE INGREDIENTS: pimavanserin tartrate 34 mg/1 1
INACTIVE INGREDIENTS: magnesium stearate; MICROCRYSTALLINE CELLULOSE; HYPROMELLOSE 2910 (15 MPA.S); titanium dioxide; FERRIC OXIDE YELLOW; FD&C BLUE NO. 1; FERROSOFERRIC OXIDE

HIGHLIGHTS OF PRESCRIBING INFORMATION

These highlights do not include all the information needed to use NUPLAZID safely and effectively. See full prescribing information for NUPLAZID.
NUPLAZID® (pimavanserin) capsules, for oral use
NUPLAZID® (pimavanserin) tablets, for oral use
Initial U.S. Approval: 2016

WARNING: INCREASED MORTALITY IN ELDERLY PATIENTS WITH DEMENTIA-RELATED PSYCHOSIS

See full prescribing information for complete boxed warning.

Elderly patients with dementia-related psychosis treated with antipsychotic drugs are at an increased risk of death.

NUPLAZID is not approved for the treatment of patients with dementia who experience psychosis unless their hallucinations and delusions are related to Parkinson's disease. (5.1)

1 INDICATIONS AND USAGE

NUPLAZID is an atypical antipsychotic indicated for the treatment of hallucinations and delusions associated with Parkinson's disease psychosis. (1)

2 DOSAGE AND ADMINISTRATION

- Recommended dose is 34 mg taken orally once daily, without titration. (2.1)
- Can be taken with or without food. (2.2)
- Capsules may be swallowed whole or opened and entire contents sprinkled over a tablespoon of certain types of soft food. (2.2)

3 DOSAGE FORMS AND STRENGTHS

- Capsules: 34 mg (3)
- Tablets: 10 mg (3)

4 CONTRAINDICATIONS

Known hypersensitivity to NUPLAZID or any of its components. (4)

5 WARNINGS AND PRECAUTIONS

- QT Interval Prolongation: Increases in QT interval; avoid use with drugs that also increase the QT interval and in patients with risk factors for prolonged QT interval. (5.2)

6 ADVERSE REACTIONS

Most common adverse reactions (≥5% and twice the rate of placebo): peripheral edema and confusional state. (6.1)

To report SUSPECTED ADVERSE REACTIONS, contact Acadia Pharmaceuticals Inc. at 1-844-422-2342 or FDA at 1-800-FDA-1088 or www.fda.gov/medwatch.

7 DRUG INTERACTIONS

- Strong CYP3A4 Inhibitors: Reduce NUPLAZID dose to 10 mg once daily. (2.3, 7.1)
- Strong or Moderate CYP3A4 Inducers: Avoid concomitant use of NUPLAZID. (2.3, 7.1)

FULL PRESCRIBING INFORMATION

WARNING: INCREASED MORTALITY IN ELDERLY PATIENTS WITH DEMENTIA-RELATED PSYCHOSIS

Elderly patients with dementia-related psychosis treated with antipsychotic drugs are at an increased risk of death. NUPLAZID is not approved for the treatment of patients with dementia who experience psychosis unless their hallucinations and delusions are related to Parkinson's disease [see Warnings and Precautions (5.1)].

1 INDICATIONS AND USAGE

NUPLAZID® is indicated for the treatment of hallucinations and delusions associated with Parkinson's disease psychosis [see Clinical Studies (14)].

2 DOSAGE AND ADMINISTRATION

2.1 Recommended Dosage

The recommended dose of NUPLAZID is 34 mg taken orally once daily, without titration.

2.2 Administration Information

NUPLAZID can be taken with or without food [see Clinical Pharmacology (12.3)].

NUPLAZID capsules can be taken whole, or opened and the entire contents sprinkled over a tablespoon (15 mL) of applesauce, yogurt, pudding, or a liquid nutritional supplement. Consume the drug/food mixture immediately without chewing; do not store for future use.

2.3 Dosage Modifications for Concomitant Use with CYP3A4 Inhibitors and Inducers

- Coadministration with Strong CYP3A4 Inhibitors
  The recommended dose of NUPLAZID when coadministered with strong CYP3A4 inhibitors is 10 mg, taken orally as one tablet once daily [see Drug Interactions (7.1)].

- Coadministration with Strong or Moderate CYP3A4 Inducers
  Avoid concomitant use of strong or moderate CYP3A4 inducers with NUPLAZID [see Drug Interactions (7.1)].

3 DOSAGE FORMS AND STRENGTHS

NUPLAZID (pimavanserin) is available as:

- 34 mg strength capsules. The capsules are opaque white and light green with "PIMA" and "34" printed in black.
- 10 mg strength tablets. The orange, round, coated tablets are debossed on one side with a "P" and "10" on the reverse side.

4 CONTRAINDICATIONS

NUPLAZID is contraindicated in patients with a history of a hypersensitivity reaction to pimavanserin or any of its components. Rash, urticaria, and reactions consistent with angioedema (e.g., tongue swelling, circumoral edema, throat tightness, and dyspnea) have been reported [see Adverse Reactions (6.2)].

5 WARNINGS AND PRECAUTIONS

5.1 Increased Mortality in Elderly Patients with Dementia-Related Psychosis

Antipsychotic drugs increase the all-cause risk of death in elderly patients with dementia-related psychosis. Analyses of 17 dementia-related psychosis placebo-controlled trials (modal duration of 10 weeks and largely in patients taking atypical antipsychotic drugs) revealed a risk of death in the drug-treated patients of between 1.6- to 1.7-times that in placebo-treated patients. Over the course of a typical 10-week controlled trial, the rate of death in drug-treated patients was about 4.5%, compared to a rate of about 2.6% in placebo-treated patients.

Although the causes of death were varied, most of the deaths appeared to be either cardiovascular (e.g., heart failure, sudden death) or infectious (e.g., pneumonia) in nature. NUPLAZID is not approved for the treatment of patients with dementia who experience psychosis unless their hallucinations and delusions are related to Parkinson's disease [see Boxed Warning].

5.2 QT Interval Prolongation

NUPLAZID prolongs the QT interval. The use of NUPLAZID should be avoided in patients with known QT prolongation or in combination with other drugs known to prolong QT interval including Class 1A antiarrhythmics (e.g., quinidine, procainamide) or Class 3 antiarrhythmics (e.g., amiodarone, sotalol), certain antipsychotic medications (e.g., ziprasidone, chlorpromazine, thioridazine), and certain antibiotics (e.g., gatifloxacin, moxifloxacin) [see Drug Interactions (7.1)]. NUPLAZID should also be avoided in patients with a history of cardiac arrhythmias, as well as other circumstances that may increase the risk of the occurrence of torsade de pointes and/or sudden death, including symptomatic bradycardia, hypokalemia or hypomagnesemia, and the presence of congenital prolongation of the QT interval [see Clinical Pharmacology (12.2)].

6 ADVERSE REACTIONS

The following serious adverse reactions are discussed elsewhere in the labeling:

- Increased Mortality in Elderly Patients with Dementia-Related Psychosis [see Boxed Warning and Warnings and Precautions (5.1)]
- QT Interval Prolongation [see Warnings and Precautions (5.2)]

6.1 Clinical Trials Experience

Because clinical trials are conducted under widely varying conditions, adverse reaction rates observed in the clinical trials of a drug cannot be directly compared to rates in the clinical trials of another drug and may not reflect the rates observed in practice.

The clinical trial database for NUPLAZID consists of over 1200 subjects and patients exposed to one or more doses of NUPLAZID. Of these, 616 were patients with hallucinations and delusions associated with Parkinson's disease psychosis (PDP). In the placebo-controlled setting, the majority of experience in patients comes from studies evaluating once-daily NUPLAZID doses of 34 mg (N=202) compared to placebo (N=231) for up to 6 weeks. In the controlled trial setting, the study population was approximately 64% male and 91% Caucasian, and the mean age was about 71 years at study entry. Additional clinical trial experience in patients with hallucinations and delusions associated with PDP comes from two open-label, safety extension studies (total N=497). The majority of patients receiving long-term treatment received 34 mg once-daily (N=459). Over 300 patients have been treated for more than 6 months; over 270 have been treated for at least 12 months; and over 150 have been treated for at least 24 months.

The following adverse reactions are based on the 6-week, placebo-controlled studies in which NUPLAZID was administered once daily to patients with hallucinations and delusions associated with PDP.

Common Adverse Reactions (incidence ≥5% and at least twice the rate of placebo): peripheral edema (7% NUPLAZID 34 mg vs. 2% placebo) and confusional state (6% NUPLAZID 34 mg vs. 3% placebo).

Adverse Reactions Leading to Discontinuation of Treatment

A total of 8% (16/202) of NUPLAZID 34 mg-treated patients and 4% (10/231) of placebo-treated patients discontinued because of adverse reactions. The adverse reactions that occurred in more than one patient and with an incidence at least twice that of placebo were hallucination (2% NUPLAZID vs. <1% placebo), urinary tract infection (1% NUPLAZID vs. <1% placebo), and fatigue (1% NUPLAZID vs. 0% placebo).

Adverse reactions that occurred in 6-week, placebo-controlled studies and that were reported at an incidence of ≥2% and >placebo are presented in Table 1.

Table 1 Adverse Reactions in Placebo-Controlled Studies of 6-Week Treatment Duration and Reported in ≥2% and >Placebo
Percentage of Patients Reporting Adverse Reaction
 | NUPLAZID 34 mg | Placebo
 | N=202 | N=231
Gastrointestinal disorders
Nausea | 7% | 4%
Constipation | 4% | 3%
General disorders
Peripheral edema | 7% | 2%
Gait disturbance | 2% | <1%
Psychiatric disorders
Hallucination | 5% | 3%
Confusional state | 6% | 3%

Adverse Reactions in Demographic Subgroups

Examination of population subgroups in the 6-week, placebo-controlled studies did not reveal any differences in safety on the basis of age (≤75 vs. >75 years) or sex. Because the study population was predominantly Caucasian (91%; consistent with reported demographics for PD/PDP), racial or ethnic differences in the safety profile of NUPLAZID could not be assessed. In addition, in the 6-week, placebo-controlled studies, no clinically relevant differences in the incidence of adverse reactions were observed among those with a Mini-Mental State Examination (MMSE) score at entry of <25 versus those with scores ≥25.

6.2 Postmarketing Experience

The following adverse reactions have been identified during postapproval use of NUPLAZID. Because these reactions are reported voluntarily from a population of uncertain size, it is not always possible to reliably estimate their frequency or establish a causal relationship to drug exposure. These reactions include rash, urticaria, reactions consistent with angioedema (e.g., tongue swelling, circumoral edema, throat tightness, and dyspnea), somnolence, falls, agitation, aggression, and fecal incontinence.

7 DRUG INTERACTIONS

7.1 Drugs Having Clinically Important Interactions with NUPLAZID

Table 2 Clinically Important Drug Interactions with NUPLAZID
QT Interval Prolongation
Clinical Impact: | Concomitant use of drugs that prolong the QT interval may add to the QT effects of NUPLAZID and increase the risk of cardiac arrhythmia.
Intervention: | Avoid the use of NUPLAZID in combination with other drugs known to prolong QT interval (e.g., Class 1A antiarrythmics, Class 3 antiarrythmics, certain antipsychotics or antibiotics) [see Warnings and Precautions (5.2)].
Strong CYP3A4 Inhibitors
Clinical Impact: | Concomitant use of NUPLAZID with a strong CYP3A4 inhibitor increases pimavanserin exposure [see Clinical Pharmacology (12.3)].
Intervention: | If NUPLAZID is used with a strong CYP3A4 inhibitor, reduce the dosage of NUPLAZID [see Dosage and Administration (2.3)].
Strong or Moderate CYP3A4 Inducers
Clinical Impact: | Concomitant use of NUPLAZID with strong or moderate CYP3A4 inducers reduces pimavanserin exposure [see Clinical Pharmacology (12.3)].
Intervention: | Avoid concomitant use of strong or moderate CYP3A4 inducers with NUPLAZID [see Dosage and Administration (2.3)].

7.2 Drugs Having No Clinically Important Interactions with NUPLAZID

Based on pharmacokinetic studies, no dosage adjustment of carbidopa/levodopa is required when administered concomitantly with NUPLAZID [see Clinical Pharmacology (12.3)].

8 USE IN SPECIFIC POPULATIONS

8.1 Pregnancy

Risk Summary

There are no data on NUPLAZID use in pregnant women that would allow assessment of the drug-associated risk of major congenital malformations or miscarriage. In animal reproduction studies, no adverse developmental effects were seen when pimavanserin was administered orally to rats or rabbits during the period of organogenesis at doses up to 10- or 12-times the maximum recommended human dose (MRHD) of 34 mg/day, respectively. Administration of pimavanserin to pregnant rats during pregnancy and lactation resulted in maternal toxicity and lower pup survival and body weight at doses which are 2-times the MRHD of 34 mg/day [see Data].

The estimated background risk of major birth defects and miscarriage for the indicated population is unknown. In the U.S. general population, the estimated background risk of major birth defects and miscarriage in clinically recognized pregnancies is 2-4% and 15-20%, respectively.

Data

Animal Data

Pimavanserin was not teratogenic in pregnant rats when administered during the period of organogenesis at oral doses of 0.9, 8.5, and 51 mg/kg/day, which are 0.2- and 10-times the MRHD of 34 mg/day based on AUC at mid and high doses, respectively. Maternal toxicity included reduction in body weight and food consumption at the highest dose.

Administration of pimavanserin to pregnant rats during pregnancy and lactation at oral doses of 8.5, 26, and 51 mg/kg/day, which are 0.14- to 14-times the MRHD of 34 mg/day based on AUC, caused maternal toxicity, including mortality, clinical signs including dehydration, hunched posture, and rales, and decreases in body weight, and/or food consumption at doses ≥26 mg/kg/day (2-times the MRHD based on AUC). At these maternally toxic doses there was a decrease in pup survival, reduced litter size, and reduced pup weights, and food consumption. Pimavanserin had no effect on sexual maturation, neurobehavioral function including learning and memory, or reproductive function in the first generation pups up to 14-times the MRHD of 34 mg/day based on AUC.

Pimavanserin was not teratogenic in pregnant rabbits during the period of organogenesis at oral doses of 4.3, 43, and 85 mg/kg/day, which are 0.2- to 12-times the MRHD of 34 mg/day based on AUC. Maternal toxicity, including mortality, clinical signs of dyspnea and rales, decreases in body weight and/or food consumption, and abortions occurred at doses 12-times the MRHD of 34 mg/day based on AUC.

8.2 Lactation

Risk Summary

There is no information regarding the presence of pimavanserin in human milk, the effects on the breastfed infant, or the effects on milk production. The developmental and health benefits of breastfeeding should be considered along with the mother's clinical need for NUPLAZID and any potential adverse effects on the breastfed infant from NUPLAZID or from the underlying maternal condition.

8.4 Pediatric Use

Safety and effectiveness of NUPLAZID have not been established in pediatric patients.

8.5 Geriatric Use

No dose adjustment is required for elderly patients.

Parkinson's disease is a disorder occurring primarily in individuals over 55 years of age. The mean age of patients enrolled in the 6-week clinical studies with NUPLAZID [see Adverse Reactions (6.1)] was 71 years, with 49% 65-75 years old and 31% >75 years old. In the pooled population of patients enrolled in 6-week, placebo-controlled studies (N=614), 27% had MMSE scores from 21 to 24 compared to 73% with scores ≥25. No clinically meaningful differences in safety or effectiveness were noted between these two groups.

8.6 Patients with Renal Impairment

No dosage adjustment for NUPLAZID is needed in patients with mild to severe renal impairment or end stage renal disease (ESRD); however, increased exposure (Cmax and AUC) to NUPLAZID occurred in patients with severe renal impairment (CrCL <30 mL/min, Cockcroft-Gault) in a renal impairment study [see Clinical Pharmacology (12.3)].

NUPLAZID should be used with caution in patients with severe renal impairment and end stage renal disease.

In a renal impairment study, dialysis did not appear to significantly affect the concentrations of NUPLAZID [see Clinical Pharmacology (12.3)].

8.7 Patients with Hepatic Impairment

No dosage adjustment for NUPLAZID is recommended in patients with hepatic impairment based on the exposure differences observed in patients with and without hepatic impairment in a hepatic impairment study [see Clinical Pharmacology (12.3)].

8.8 Other Specific Populations

No dosage adjustment is required based on patient's age, sex, ethnicity, or weight. These factors do not affect the pharmacokinetics of NUPLAZID [see Clinical Pharmacology (12.3)].

9 DRUG ABUSE AND DEPENDENCE

9.1 Controlled Substance

NUPLAZID is not a controlled substance.

9.2 Abuse

NUPLAZID has not been systematically studied in humans for its potential for abuse, tolerance, or physical dependence.

While short-term, placebo-controlled and long-term, open-label clinical trials did not reveal increases in drug-seeking behavior, the limited experience from the clinical trials do not predict the extent to which a CNS-active drug will be misused, diverted, and/or abused once marketed.

10 OVERDOSAGE

10.1 Human Experience

The pre-marketing clinical trials involving NUPLAZID in approximately 1200 subjects and patients do not provide information regarding symptoms with overdose. In healthy subject studies, dose-limiting nausea and vomiting were observed.

10.2 Management of Overdose

There are no known specific antidotes for NUPLAZID. In managing overdose, cardiovascular monitoring should commence immediately and should include continuous ECG monitoring to detect possible arrhythmias [see Warnings and Precautions (5.2)]. If antiarrhythmic therapy is administered, disopyramide, procainamide, and quinidine should not be used, as they have the potential for QT-prolonging effects that might be additive to those of NUPLAZID [see Drug Interactions (7.1)]. Consider the long plasma half-life of pimavanserin (about 57 hours) and the possibility of multiple drug involvement. Consult a Certified Poison Control Center (1-800-222-1222) for up-to-date guidance and advice.

11 DESCRIPTION

NUPLAZID contains pimavanserin, an atypical antipsychotic, which is present as pimavanserin tartrate salt with the chemical name, urea, N-[(4-fluorophenyl)methyl]-N-(1-methyl-4-piperidinyl)-N'-[[4-(2-methylpropoxy)phenyl]methyl]-,(2R,3R)-2,3-dihydroxybutanedioate (2:1). Pimavanserin tartrate is freely soluble in water. Its molecular formula is (C25H34FN3O2)2∙C4H6O6 and its molecular weight is 1005.20 (tartrate salt). The chemical structure is:

The molecular formula of pimavanserin free base is C25H34FN3O2 and its molecular weight is 427.55.

NUPLAZID capsules are intended for oral administration only. Each capsule contains 40 mg of pimavanserin tartrate, which is equivalent to 34 mg of pimavanserin free base. Inactive ingredients include magnesium stearate and microcrystalline cellulose. Additionally, the following inactive ingredients are present as components of the capsule shell: black iron oxide, FD&C blue #1, hypromellose, titanium dioxide, and yellow iron oxide.

NUPLAZID tablets are intended for oral administration only. Each round, orange, immediate-release, film coated tablet contains 11.8 mg of pimavanserin tartrate, which is equivalent to 10 mg pimavanserin free base. Inactive ingredients include magnesium stearate, pregelatinized starch, and silicified microcrystalline cellulose. Additionally, the following inactive ingredients are present as components of the film coat: polyethylene glycol, polyvinyl alcohol, red iron oxide, talc, titanium dioxide, and yellow iron oxide.

12 CLINICAL PHARMACOLOGY

12.1 Mechanism of Action

The mechanism of action of pimavanserin in the treatment of hallucinations and delusions associated with PDP is unclear. However, the effect of pimavanserin could be mediated through a combination of inverse agonist and antagonist activity at serotonin 5-HT2A receptors and to a lesser extent at serotonin 5-HT2C receptors.

12.2 Pharmacodynamics

In vitro, pimavanserin acts as an inverse agonist and antagonist at serotonin 5-HT2A receptors with high binding affinity (Ki value 0.087 nM) and at serotonin 5-HT2C receptors with lower binding affinity (Ki value 0.44 nM). Pimavanserin shows low binding to sigma 1 receptors (Ki value 120 nM) and has no appreciable affinity (Ki value >300 nM), to serotonin 5-HT2B, dopaminergic (including D2), muscarinic, histaminergic, or adrenergic receptors, or to calcium channels.

Cardiac Electrophysiology

The effect of NUPLAZID on the QTc interval was evaluated in a randomized placebo- and positive-controlled double-blind, multiple-dose parallel thorough QTc study in 252 healthy subjects. A central tendency analysis of the QTc data at steady-state demonstrated that the maximum mean change from baseline (upper bound of the two-sided 90% CI) was 13.5 (16.6) msec at a dose of twice the therapeutic dose. A pharmacokinetic/ pharmacodynamic analysis with NUPLAZID suggested a concentration-dependent QTc interval prolongation in the therapeutic range.

In the 6-week, placebo-controlled effectiveness studies, mean increases in QTc interval of ~5-8 msec were observed in patients receiving once-daily doses of NUPLAZID 34 mg. These data are consistent with the profile observed in a thorough QT study in healthy subjects. Sporadic QTcF values ≥500 msec and change from baseline values ≥60 msec were observed in subjects treated with NUPLAZID 34 mg; although the incidence was generally similar for NUPLAZID and placebo groups. There were no reports of torsade de pointes or any differences from placebo in the incidence of other adverse reactions associated with delayed ventricular repolarization in studies of NUPLAZID, including those patients with hallucinations and delusions associated with PDP [see Warnings and Precautions (5.2)].

12.3 Pharmacokinetics

Pimavanserin demonstrates dose-proportional pharmacokinetics after single oral doses from 17 to 255 mg (0.5- to 7.5-times the recommended dosage). The pharmacokinetics of pimavanserin are similar in both the study population and healthy subjects. The mean plasma half-lives for pimavanserin and the active metabolite (N-desmethylated metabolite) are approximately 57 hours and 200 hours, respectively.

Absorption

The median Tmax of pimavanserin was 6 (range 4-24) hours and was generally unaffected by dose. The bioavailability of pimavanserin oral tablet and pimavanserin solution was essentially identical. The formation of the major circulating N-desmethylated metabolite AC-279 (active) from pimavanserin occurs with a median Tmax of 6 hours.

Effect of Food

Ingestion of a high-fat meal had no significant effect on rate (Cmax) and extent (AUC) of pimavanserin exposure. Cmax decreased by about 9% while AUC increased by about 8% with a high-fat meal.

Distribution

Pimavanserin is highly protein bound (~95%) in human plasma. Protein binding appeared to be dose-independent and did not change significantly over dosing time from Day 1 to Day 14. Following administration of a single dose of NUPLAZID (34 mg), the mean (SD) apparent volume of distribution was 2173 (307) L.

Elimination

Metabolism

Pimavanserin is predominantly metabolized by CYP3A4 and CYP3A5 and to a lesser extent by CYP2J2, CYP2D6, and various other CYP and FMO enzymes. CYP3A4 is the major enzyme responsible for the formation of its major active metabolite (AC-279). Pimavanserin does not cause clinically significant CYP inhibition or induction of CYP3A4. Based on in vitro data, pimavanserin is not an irreversible inhibitor of any of the major hepatic and intestinal human CYP enzymes involved in drug metabolism (CYP1A2, 2B6, 2C8, 2C9, 2C19, 2D6, and 3A4).

Based on in vitro studies, transporters play no significant role in the disposition of pimavanserin.

AC-279 is neither a reversible or irreversible (metabolism-dependent) inhibitor of any of the major hepatic and intestinal human CYP enzymes involved in drug metabolism (CYP1A2, 2B6, 2C8, 2C9, 2C19, 2D6, and 3A4). AC-279 does not cause clinically significant CYP3A induction and is not predicted to cause induction of any other CYP enzymes involved in drug metabolism.

Excretion

Approximately 0.55% of the 34 mg oral dose of ^14C-pimavanserin was eliminated as unchanged drug in urine and 1.53% was eliminated in feces after 10 days.

Less than 1% of the administered dose of pimavanserin and its active metabolite AC-279 were recovered in urine.

Specific Populations

Population PK analysis indicated that age, sex, ethnicity, and weight do not have clinically relevant effect on the pharmacokinetics of pimavanserin. In addition, the analysis indicated that exposure of pimavanserin in patients with mild to moderate renal impairment was similar to exposure in patients with normal renal function.

The effects of other intrinsic factors on pimavanserin pharmacokinetics is shown in Figure 1 [see Use in Specific Populations (8.6, 8.7)].

Figure 1 Effects of Intrinsic Factors on Pimavanserin Pharmacokinetics

*Less than 10% of the administered dose of NUPLAZID was recovered in the dialysate.

Drug Interaction Studies

CYP3A4 Inhibitor: ketoconazole, a strong inhibitor of CYP3A4, increased pimavanserin Cmax by 1.5-fold and AUC by 3-fold. Population PK modeling and simulation show that steady-state exposure (Cmax,ss and AUCtau) for 10 mg pimavanserin with ketoconazole is similar to exposure for 34 mg pimavanserin alone [see Dosage and Administration (2.3) and Drug Interactions (7.1)].

CYP3A4 Inducer: In a clinical study where single doses of 34 mg pimavanserin were administered on Days 1 and 22, and 600 mg rifampin, a strong inducer of CYP3A4, was given daily on Days 15 through 21, pimavanserin Cmax and AUC decreased by 71% and 91%, respectively, compared to pre-rifampin plasma concentrations. In a simulation with a moderate CYP3A4 inducer (efavirenz), physiologically based pharmacokinetic (PBPK) models predicted pimavanserin Cmax,ss and AUCtau at steady state decreased by approximately 60% and 70%, respectively [see Dosage and Administration (2.3) and Drug Interactions (7.1)].

There is no effect of pimavanserin on the pharmacokinetics of midazolam, a CYP3A4 substrate, or carbidopa/levodopa as shown in Figure 2.

Figure 2 Effects of Pimavanserin on the Pharmacokinetics of Other Drugs

*AUC and Cmax depict levodopa levels.

13 NONCLINICAL TOXICOLOGY

13.1 Carcinogenesis, Mutagenesis, Impairment of Fertility

Carcinogenesis

There was no increase in the incidence of tumors following daily oral administration of pimavanserin to mice or rats for 2 years. Mice were administered pimavanserin at oral doses of 2.6, 6, and 13 (males)/8.5, 21, and 43 mg/kg/day (females) which are 0.01- to 1- (males)/0.5- to 7- (females) times the MRHD of 34 mg/day based on AUC. Rats were administered pimavanserin at oral doses of 2.6, 8.5, and 26 (males)/4.3, 13, and 43 mg/kg/day (females) which are 0.01- to 4- (males)/0.04- to 16- (females) times the MRHD of 34 mg/day based on AUC.

Mutagenesis

Pimavanserin was not mutagenic in the in vitro Ames reverse mutation test, or in the in vitro mouse lymphoma assay, and was not clastogenic in the in vivo mouse bone marrow micronucleus assay.

Impairment of Fertility

Pimavanserin was administered orally to male and female rats before mating, through mating, and up to Day 7 of gestation at doses of 8.5, 51, and 77 mg/kg/day, which are approximately 2-, 15-, and 22-times the MRHD of 34 mg/day based on mg/m^2, respectively. Pimavanserin had no effect on fertility or reproductive performance in male and female rats at doses up to 22-times the MRHD of 34 mg based on mg/m^2. Changes in uterine parameters (decreases in the number of corpora lutea, number of implants, viable implants, and increases in pre-implantation loss, early resorptions and post-implantation loss) occurred at the highest dose which was also a maternally toxic dose. Changes in sperm parameters (decreased density and motility) and microscopic findings of cytoplasmic vacuolation in the epididymis occurred at doses approximately 15-times the MRHD of 34 mg/day based on mg/m^2.

13.2 Animal Toxicology and/or Pharmacology

Phospholipidosis (foamy macrophages and/or cytoplasmic vacuolation) was observed in multiple tissues and organs of mice, rats, and monkeys following oral daily administration of pimavanserin. The occurrence of phospholipidosis was both dose- and duration-dependent. The most severely affected organs were the lungs and kidneys. In rats, diffuse phospholipidosis was associated with increased lung and kidney weights, respiratory-related clinical signs including rales, labored breathing, and gasping, renal tubular degeneration, and, in some animals, focal/multifocal chronic inflammation in the lungs at exposures ≥10-times those at the MRHD of 34 mg/day based on AUC. Phospholipidosis caused mortality in rats at exposures ≥16-times the MRHD of 34 mg/day based on AUC. The chronic inflammation in the rat lung was characterized by minimal to mild focal collagen positive fibroplasia as shown by specialized staining. Chronic inflammation of the lungs was not seen in monkeys treated for 12 months (exposures 9-times the MRHD). Based on the exposures at the estimated No Observed Effect Level (NOEL) for chronic lung inflammation in rats, there is a 5- to 9-times safety margin after 6-months of treatment and a 2- to 4-times safety margin after 24-months (lifetime) treatment compared to exposure at the MRHD. The relevance of these findings to human risk is not clear.

14 CLINICAL STUDIES

The efficacy of NUPLAZID 34 mg as a treatment of hallucinations and delusions associated with Parkinson's disease (PD) psychosis was demonstrated in a 6-week, randomized, placebo-controlled, parallel-group study. In this outpatient study, 199 patients were randomized in a 1:1 ratio to NUPLAZID 34 mg or placebo once daily. Study patients (male or female and aged 40 years or older) had a diagnosis of PD (with or without dementia) established at least 1 year prior to study entry and had psychotic symptoms (hallucinations and/or delusions) that started after the PD diagnosis and that were severe and frequent enough to warrant treatment with an antipsychotic. At entry, patients were required to have a Mini-Mental State Examination (MMSE) score ≥21 and to be able to self-report symptoms. The majority of patients were on PD medications at entry; these medications were required to be stable for at least 30 days prior to study start and throughout the study period.

The PD-adapted Scale for the Assessment of Positive Symptoms (SAPS-PD) was used to evaluate the efficacy of NUPLAZID 34 mg. SAPS-PD is a 9-item scale adapted for PD from the Hallucinations and Delusions domains of the SAPS. Each item is scored on a scale of 0-5, with 0 being none and 5 representing severe and frequent symptoms. Therefore, the SAPS-PD total score can range from 0 to 45 with higher scores reflecting greater severity of illness. A negative change in score indicates improvement. Primary efficacy was evaluated based on change from baseline to Week 6 in SAPS-PD total score.

As shown in Table 3, Figure 3, and Figure 4, NUPLAZID 34 mg (n=95) was statistically significantly superior to placebo (n=90) in decreasing the frequency and/or severity of hallucinations and delusions in patients with PDP as measured by central, independent, and blinded raters using the SAPS-PD scale. An effect was seen on both the hallucinations and delusions components of the SAPS-PD.

Table 3 Primary Efficacy Analysis Result Based on SAPS-PD (N=185)
Endpoint | Treatment Group | Mean Baseline Score (SD) | LS Mean Change from Baseline (SE) | Placebo-subtracted Difference [Difference (drug minus placebo) in least-squares mean change from baseline.] (95% CI)
SAPS-PD | NUPLAZID | 15.9 (6.12) | -5.79 (0.66) | -3.06 [Statistically significantly superior to placebo.] (-4.91, -1.20)
SAPS-PD | Placebo | 14.7 (5.55) | -2.73 (0.67) | --
SAPS-PD Hallucinations [Supportive analysis.] | NUPLAZID | 11.1 (4.58) | -3.81 (0.46) | -2.01 (-3.29, -0.72)
SAPS-PD Hallucinations [Supportive analysis.] | Placebo | 10.0 (3.80) | -1.80 (0.46) | --
SAPS-PD Delusions | NUPLAZID | 4.8 (3.59) | -1.95 (0.32) | -0.94 (-1.83, -0.04)
SAPS-PD Delusions | Placebo | 4.8 (3.82) | -1.01 (0.32) | --
SD: standard deviation; SE: standard error; LS Mean: least-squares mean; CI: confidence interval.

The effect of NUPLAZID on SAPS-PD improved through the six-week trial period, as shown in Figure 3.

Figure 3 SAPS-PD Change from Baseline through 6 Weeks Total Study Treatment

Figure 4 Proportion of Patients with SAPS-PD Score Improvement at the End of Week 6 (N=185)

Complete response = SAPS-PD score reduced to zero from baseline value.

Patients with missing values were counted as non-responders.

Motor Function in Patients with Hallucinations and Delusions Associated with Parkinson's Disease Psychosis

NUPLAZID 34 mg did not show an effect compared to placebo on motor function, as measured using the Unified Parkinson's Disease Rating Scale Parts II and III (UPDRS Parts II+III) (Figure 5). A negative change in score indicates improvement. The UPDRS Parts II+III was used to assess the patient's Parkinson's disease state during the 6-week double-blind treatment period. The UPDRS score was calculated as the sum of the 40 items from activities of daily living and motor examination, with a range of 0 to 160.

Figure 5 Motor Function Change from Baseline to Week 6 in UPDRS Parts II+III (LSM - SE)

LSM: least-squares mean; SE: standard error. The error bars extend one SE below the LSM.

16 HOW SUPPLIED/STORAGE AND HANDLING

NUPLAZID (pimavanserin) is available as:

34 mg Capsule:

Opaque white and light green capsule with "PIMA" and "34" printed in black.

Bottle of 30: NDC 63090-340-30

10 mg Tablet:

Orange, round, coated tablet debossed with "P" on one side and "10" on the reverse.

Bottle of 30: NDC 63090-100-30

Storage

34 mg Capsule:

Store at 20°C to 25°C (68°F to 77°F); excursions permitted between 15°C and 30°C (59°F and 86°F) [See USP Controlled Room Temperature]. To prevent potential capsule color fading, protect from light.

10 mg Tablet:

Store at 20°C to 25°C (68°F to 77°F); excursions permitted between 15°C and 30°C (59°F and 86°F) [See USP Controlled Room Temperature].

17 PATIENT COUNSELING INFORMATION

Concomitant Medication

Advise patients to inform their healthcare providers if there are any changes to their current prescription or over-the-counter medications, since there is a potential for drug interactions [see Warnings and Precautions (5.2), Drug Interactions (7)].

Administration Instructions

Advise patients to take the capsule whole or sprinkled over a tablespoon (15 mL) of applesauce, yogurt, pudding, or a liquid nutritional supplement. Advise patients to consume the drug/food mixture immediately and not to store for future use [see Dosage and Administration (2.2)].

Distributed by:
Acadia Pharmaceuticals Inc.
San Diego, CA 92130 USA

NUPLAZID® is a registered trademark of Acadia Pharmaceuticals Inc.
©2025 Acadia Pharmaceuticals Inc. All rights reserved.

PRINCIPAL DISPLAY PANEL - 34 mg Capsule Bottle Label

NDC 63090-340-30

34 mg

NUPLAZID®
(pimavanserin) capsules

34 mg per capsule

Rx only
30 Capsules

PRINCIPAL DISPLAY PANEL - 10 mg Tablet Bottle Label

NDC 63090-100-30

10 mg

NUPLAZID®
(pimavanserin) tablets

10 mg per tablet

Rx only
30 Tablets